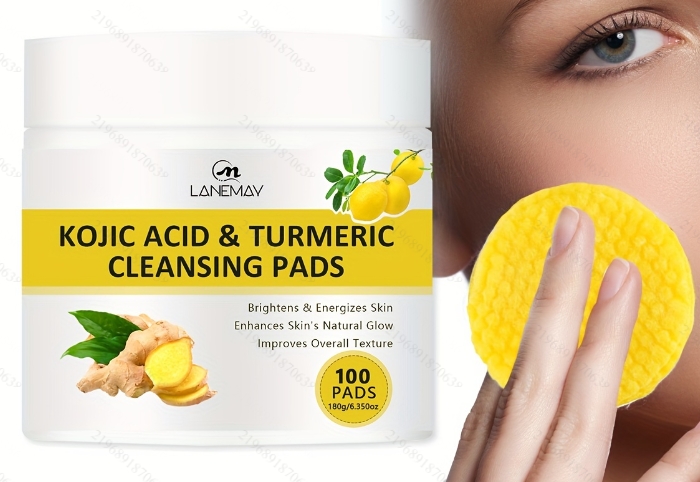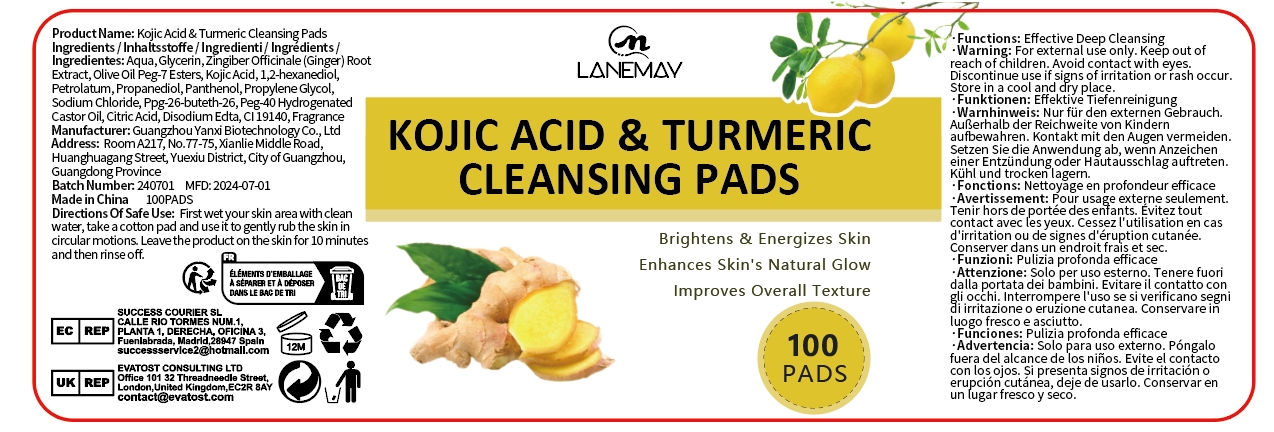 DRUG LABEL: Kojic Acid  Turmeric Cleansing Pads
NDC: 84025-275 | Form: FILM
Manufacturer: Guangzhou Yanxi Biotechnology Co., Ltd
Category: otc | Type: HUMAN OTC DRUG LABEL
Date: 20241127

ACTIVE INGREDIENTS: GLYCERIN 9 mg/180 g; PANTHENOL 7 mg/180 g
INACTIVE INGREDIENTS: WATER

DOSAGE AND ADMINISTRATION

First wet your skin area with clean water, take a cotton pad and use it to gently rub the skin incircular motions. Leave the product on the skin for 10 minute and then rinse off.

WARNINGS

Keep out of children

INACTIVE INGREDIENT

Aqua

INDICATIONS AND USAGE

For daily skin clean

Keep out of children

PURPOSE

Brightens and eEnergizes skin